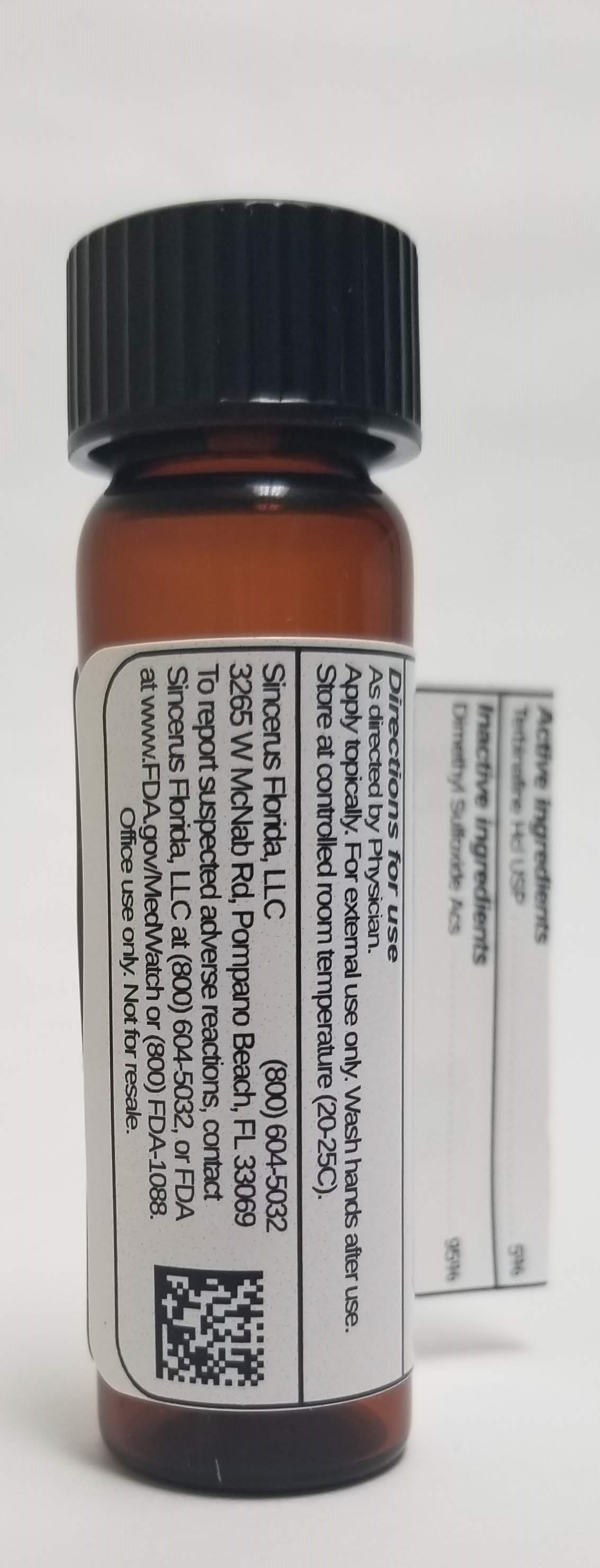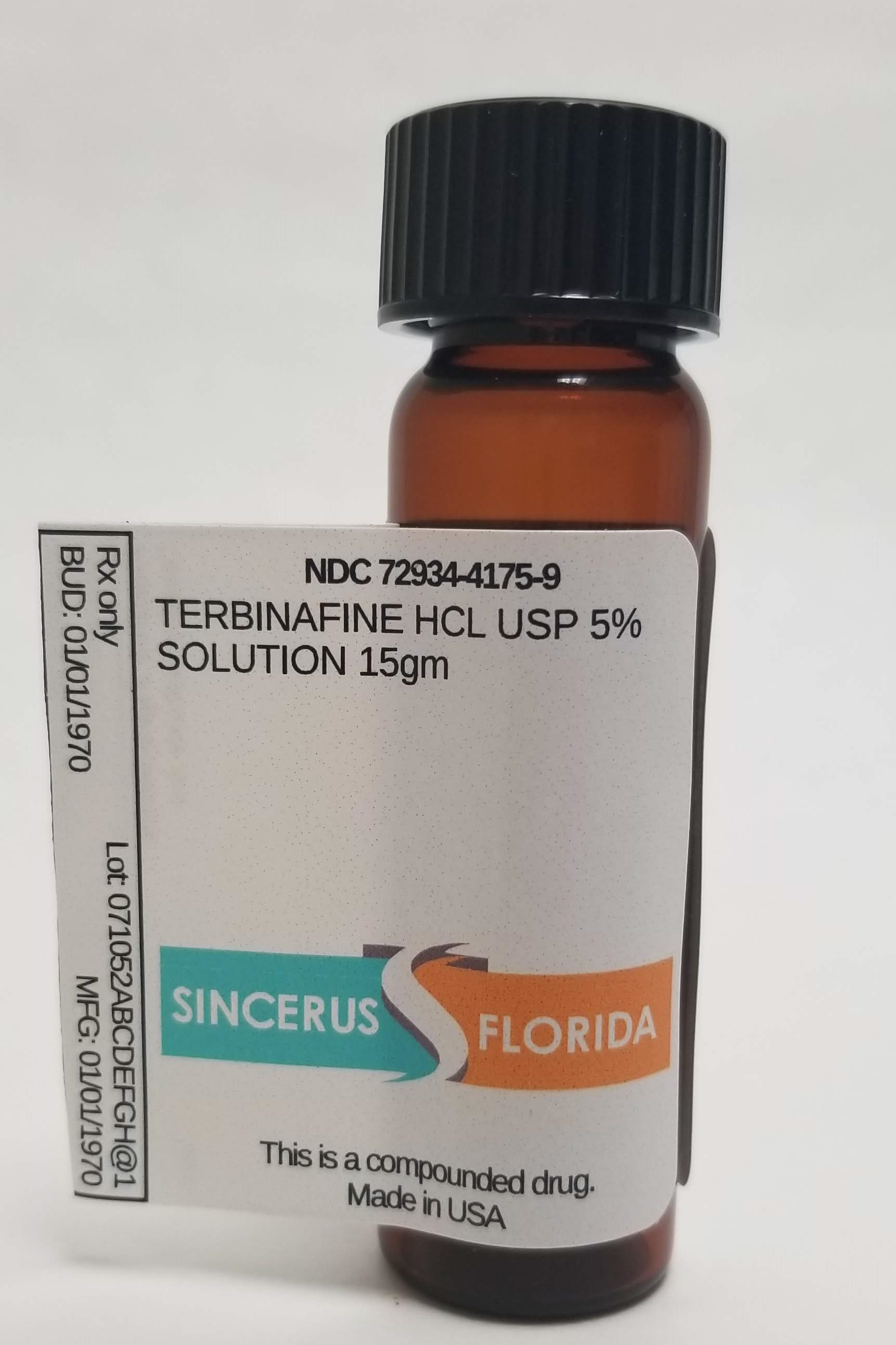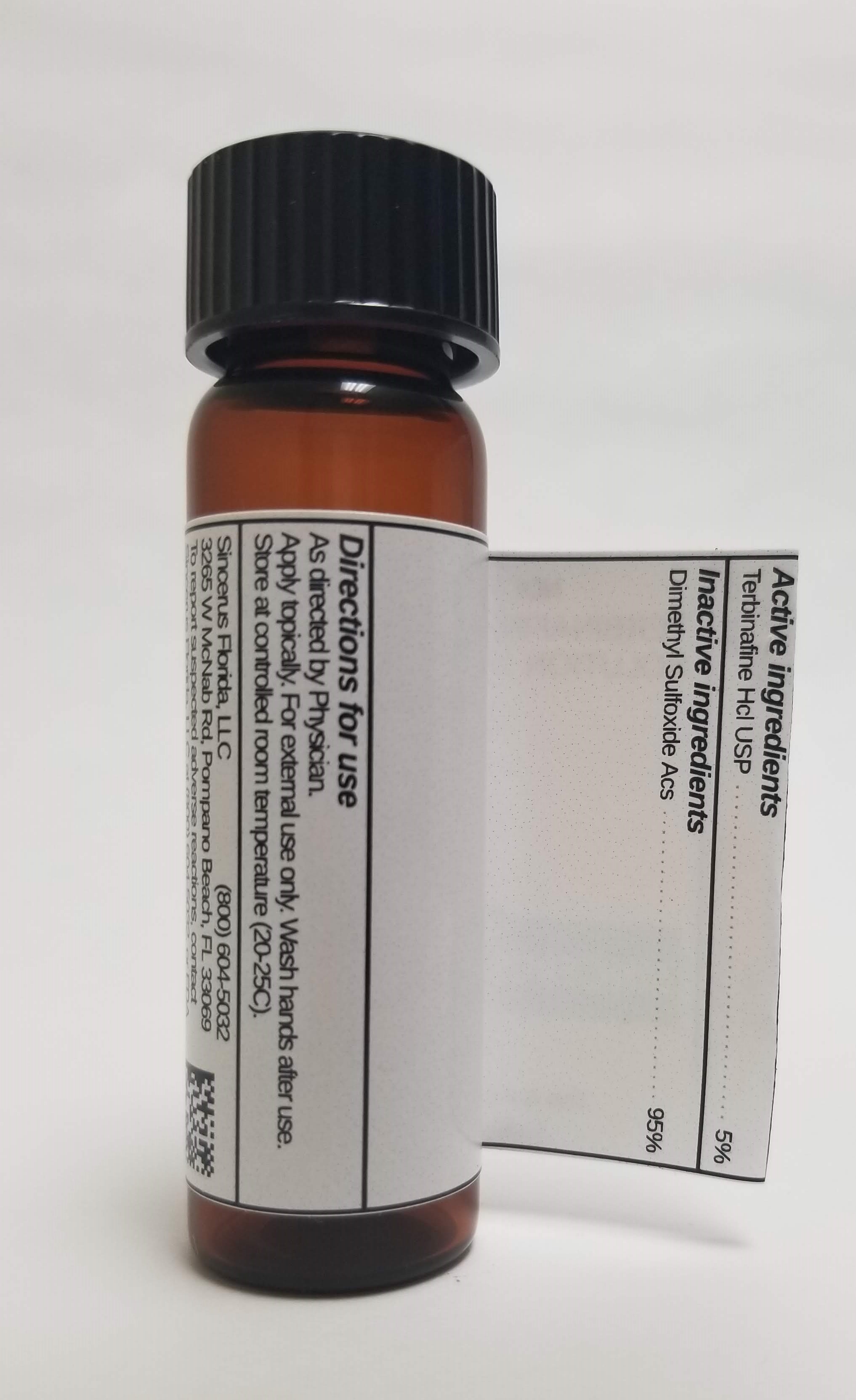 DRUG LABEL: TERBINAFINE HCL 5%
NDC: 72934-4175 | Form: SOLUTION
Manufacturer: Sincerus Florida, LLC
Category: prescription | Type: HUMAN PRESCRIPTION DRUG LABEL
Date: 20190521

ACTIVE INGREDIENTS: TERBINAFINE HYDROCHLORIDE 5 g/100 g

TERBINAFINE HCL 5%